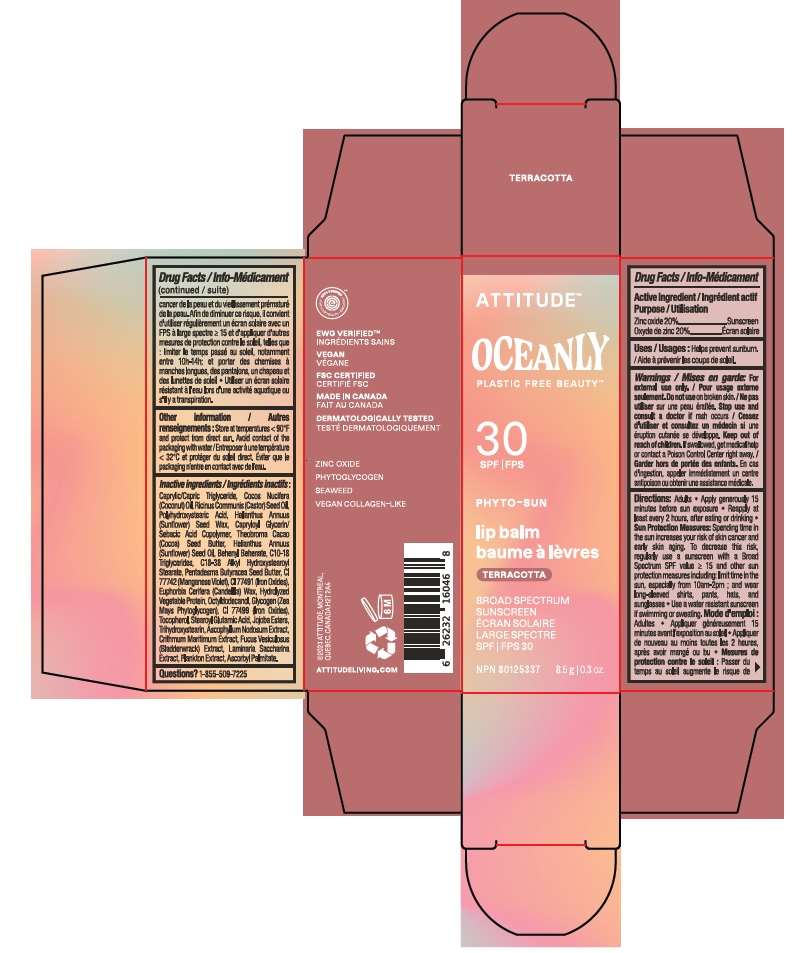 DRUG LABEL: ATTITUDE Oceanly Phyto-sun lip balm SPF 30 Terracotta
NDC: 61649-046 | Form: STICK
Manufacturer: 9055-7588 Quebec Inc. DBA Attitude
Category: otc | Type: HUMAN OTC DRUG LABEL
Date: 20251020

ACTIVE INGREDIENTS: ZINC OXIDE 20 g/100 g
INACTIVE INGREDIENTS: TETRASELMIS SUECICA; PENTADESMA BUTYRACEA WHOLE; HYDROLYZED SOY PROTEIN (ENZYMATIC; 2000 MW); TRIHYDROXYSTEARIN; SACCHARINA LATISSIMA; SUNFLOWER OIL; JOJOBA OIL; CRITHMUM MARITIMUM; COCOA BUTTER; HELIANTHUS ANNUUS SEED WAX; CAPRYLOYL GLYCERIN/SEBACIC ACID COPOLYMER (2000 MPA.S); BEHENYL BEHENATE; CORN; GLYCOGEN; FUCUS VESICULOSUS; ASCORBYL PALMITATE; FERRIC OXIDE RED; FERROSOFERRIC OXIDE; ASCOPHYLLUM NODOSUM; C18-38 ALKYL HYDROXYSTEAROYL STEARATE; CASTOR OIL; POLYHYDROXYSTEARIC ACID (2300 MW); MEDIUM-CHAIN TRIGLYCERIDES; COCONUT OIL; C10-18 TRIGLYCERIDES; MANGANESE VIOLET; .ALPHA.-TOCOPHEROL; HYDROLYZED WHEAT PROTEIN (ENZYMATIC, 3000 MW); OCTYLDODECANOL; CANDELILLA WAX; STEAROYL GLUTAMIC ACID

ATTITUDE Oceanly Phyto-sun lip balm SPF 30 Terracotta

Drug facts

ACTIVE INGREDIENT

Zinc oxide (20 %)

PURPOSE

Sunscreen

INDICATIONS AND USAGE

Helps prevent sunburn.

WARNINGS

For external use only.

Do not use on broken skin.

Keep out of reach of children. If swallowed, get medical help or contact a Poison Control Center right away.

Stop use and consult a doctor if rash occurs.

DOSAGE AND ADMINISTRATION

Adults.

- Apply generously 15 minutes before sun exposure.
- Reapply at least every 2 hours, after eating or drinking.
- Sun Protection Measures: Spending time in the sun increases your risk of skin cancer and early aging. To decrease this risk, regularly use a sunscreen with a Broad Spectrum SPFvalue of 15 or higher and other sun protection measures including: limit time in the sun, especially from 10am-2pm; and wear long-sleeved shirts, pants, hats and sunglasses.
- Use a water resistant sunscreen if swimming or sweating.

INACTIVE INGREDIENT

Caprylic/Capric Triglyceride, Cocos Nucifera (Coconut) Oil, Ricinus Communis (Castor) Seed Oil, Polyhydroxystearic Acid, Helianthus Annuus (Sunflower) Seed Wax, Capryloyl Glycerin/Sebacic Acid Copolymer, Theobroma Cacao (Cocoa) Seed Butter, Helianthus Annuus (Sunflower) Seed Oil, Behenyl Behenate, C10-18 Triglycerides, C18-38 Alkyl Hydroxystearoyl Stearate, Pentadesma Butyracea Seed Butter, CI 77742 (Manganese Violet), CI 77491 (Iron Oxides), Euphorbia Cerifera (Candelilla) Wax, Hydrolyzed Vegetable Protein, Octyldodecanol, Glycogen (Zea Mays Phytoglycogen), CI 77499 (Iron Oxides), Tocopherol, Stearoyl Glutamic Acid, Jojoba Esters, Trihydroxystearin, Ascophyllum Nodosum Extract, Crithmum Maritimum Extract, Fucus Vesiculosus (Bladderwrack) Extract, Laminaria Saccharina Extract, Plankton Extract, Ascorbyl Palmitate.

STORAGE AND HANDLING

Store at temperatures < 90F and protect from direct sun. Avoid contact of packaging with water.

Questions ? 1-855-509-7225

PACKAGE LABEL

ATTITUDETM

SPF 30

OCEANLY PLASTIC FREE BEAUTYTM

PHYTO-SUN

Lip balm

Terracotta

Broad spectrum sunscreen

Zinc oxide

Phytoglycogen

Seaweed

Vegan collagen-like

NPN 80125337

8.5 g /0.3 oz.

EWG Verified

Vegan

FSC Certified

Made in Canada

Dermatologically tested